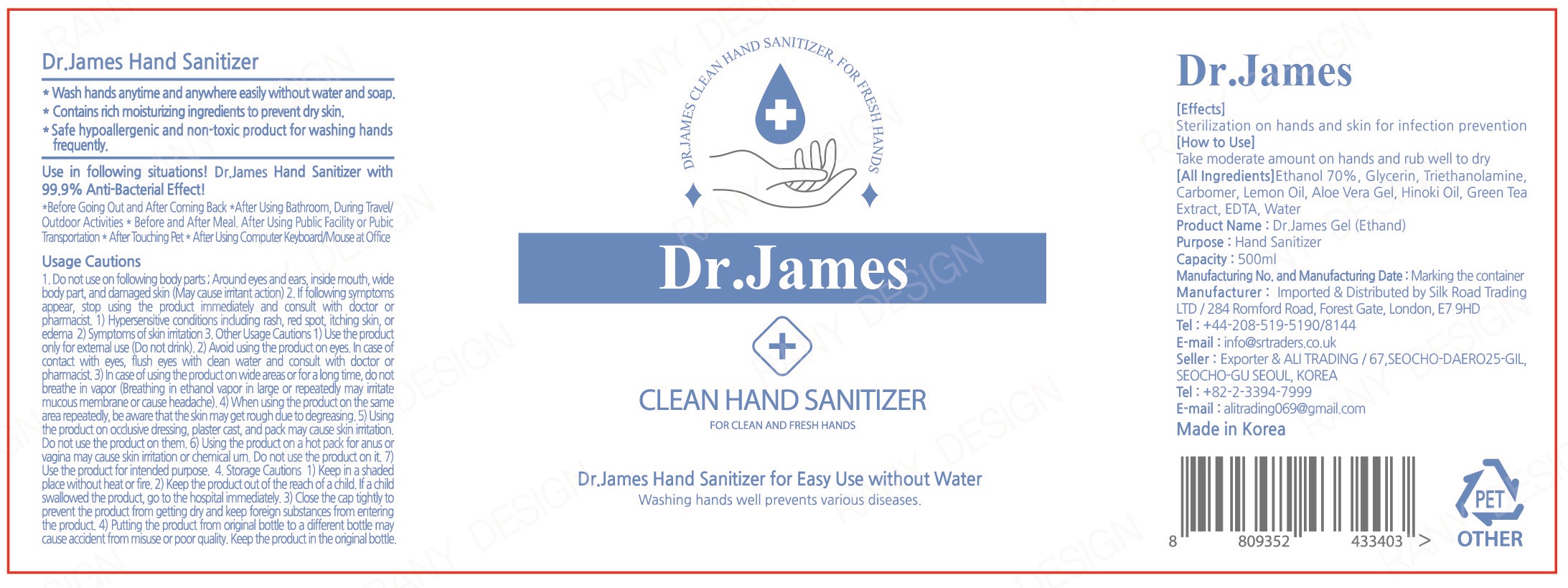 DRUG LABEL: Dr. James Gel (Ethanol)
NDC: 73065-0005 | Form: GEL
Manufacturer: WOORILIFE&HEALTH
Category: otc | Type: HUMAN OTC DRUG LABEL
Date: 20200626

ACTIVE INGREDIENTS: ALCOHOL 70 mL/100 mL
INACTIVE INGREDIENTS: ALOE VERA LEAF; TROLAMINE; CARBOMER HOMOPOLYMER, UNSPECIFIED TYPE; GLYCERIN; EDETIC ACID; LEMON OIL; GREEN TEA LEAF

Woorilife&Health - Dr.James Gel

ACTIVE INGREDIENT

alcohol

INACTIVE INGREDIENT

glycerin, triethanolamine, carbomer, lemon oil, aloe vera gel, hinoki oil, green tea extract, edta, water

PURPOSE

antiseptic

KEEP OUT OF REACH OF CHILDREN

Take moderate amount on hands and rub well to dry

INDICATIONS AND USAGE

- Adults and children 2 years of age and older

Brush teeth thoroughly preferably after each meal or at least twice a day or as directed by a dentist or docter.

- Children under 6 years

To minimize swallowing, use a pea-sized amount and supervise brushing until good habits are established.

- Children under 2 years

Consult a dentist or doctor

WARNINGS

1) Be careful not to swallow it, and rinse your mouth thoroughly after use.

2) If any abnormalities such as gum or mouth damage are caused by using this toothpaste, stop using the product and consult a doctor or dentist.

3) For children under 6 years of age, use a small amount of pea toothpaste per serving and use it under the supervision of a guardian to avoid sucking or swallowing.

4) If a child under 6 years of age swallows a large amount, consult a doctor or dentist immediately.

5) Keep out of reach of children under 6 years old.

DOSAGE AND ADMINISTRATION

for external use only